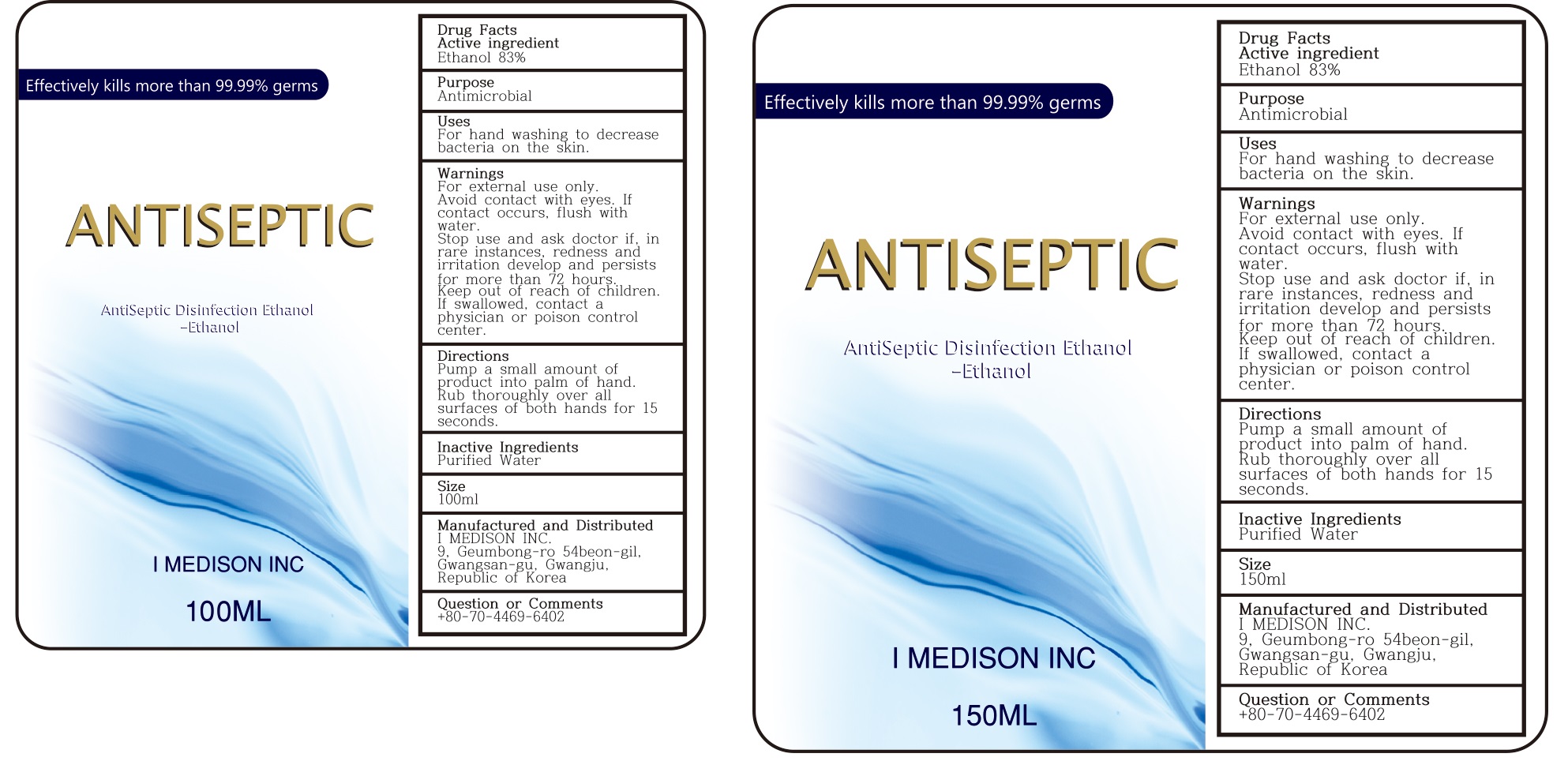 DRUG LABEL: ANTISEPTIC
NDC: 74650-0001 | Form: LIQUID
Manufacturer: I MEDISON CO., LTD.
Category: otc | Type: HUMAN OTC DRUG LABEL
Date: 20200413

ACTIVE INGREDIENTS: ALCOHOL 83 mL/100 mL
INACTIVE INGREDIENTS: WATER

Drug Facts

ACTIVE INGREDIENT

alcohol

INACTIVE INGREDIENT

Water

PURPOSE

to desrease bacteria on hands.

KEEP OUT OF REACH OF THE CHILDREN

INDICATIONS AND USAGE

Pump a small amount of product into palm of hand.
Rub thoroughly over all surfaces of both hands for 15 seconds.

WARNINGS

■ Flammable. Keep away from fire or flame.

■ For external use only.

■ Do not use in eyes.

■ lf swallowed, get medical help promptly.

■ Stop use, ask doctor lf irritation occurs.

■ Keep out of reach of children.

DOSAGE AND ADMINISTRATION

for external use only